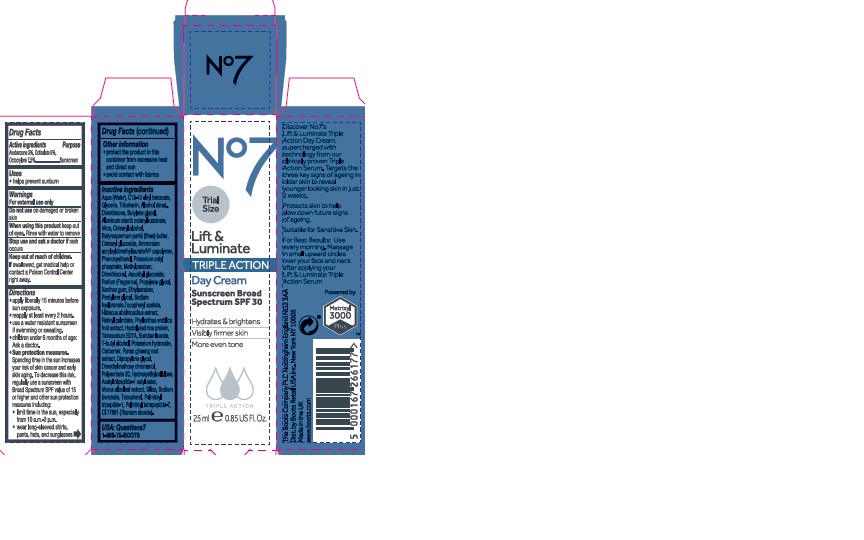 DRUG LABEL: No7 Lift and Luminate Triple Action Day Cream SPF 30
NDC: 11489-137 | Form: CREAM
Manufacturer: BCM Ltd
Category: otc | Type: HUMAN OTC DRUG LABEL
Date: 20200123

ACTIVE INGREDIENTS: AVOBENZONE 0.75 g/25 g; OCTOCRYLENE 1.875 g/25 g; OCTISALATE 1.25 g/25 g
INACTIVE INGREDIENTS: WATER; GLYCERIN; ALUMINUM STARCH OCTENYLSUCCINATE; DIMETHICONE; MICA; ALKYL (C12-15) BENZOATE; CETEARYL GLUCOSIDE; TRIBEHENIN; PENTYLENE GLYCOL; AMMONIUM ACRYLOYLDIMETHYLTAURATE/VP COPOLYMER; PHENOXYETHANOL; CETOSTEARYL ALCOHOL; SHEA BUTTER; BUTYLENE GLYCOL; METHYLPARABEN; DIMETHICONOL (40 CST); ETHYLPARABEN; XANTHAN GUM; SODIUM LAUROYL LACTYLATE; PHYLLANTHUS EMBLICA FRUIT; VITAMIN A PALMITATE; PANAX GINSENG ROOT WATER; ASCORBYL GLUCOSIDE; EDETATE SODIUM; TERT-BUTYL ALCOHOL; PROPYLENE GLYCOL; POLYSORBATE 20; CARBOMER 940; DIPROPYLENE GLYCOL; DIMETHYLMETHOXY CHROMANOL; POTASSIUM HYDROXIDE; N-ACETYL DIPEPTIDE-1; TOCOPHEROL; MORUS ALBA LEAF; SODIUM BENZOATE; TITANIUM DIOXIDE; PALMITOYL TETRAPEPTIDE-7; PALMITOYL TRIPEPTIDE-1

No7 Lift and Luminate Triple Action Day Cream Sunscreen Broad Spectrum SPF 30

Carton Active Ingredients Section

Active ingredients

Avobenzone 3%

Octisalate 5%

Octocrylene 7.5%

Uses

Uses - helps prevent sunburn

Warnings

For external use only

Do not use on damaged or broken skin

When using this product keep out of eyes. Rinse with water to remove.

Ask a doctor

Stop use and ask a doctor if rash occurs

Keep out of reach of children

If swallowed, get medical help or contact a Poison Control Center right away

Directions

Apply liberally 15 minutes before sun exposure

reapply at least every 2 hours

use a water resistant sunscreen if swimming or sweating

children under 6 months of age: Ask a doctor

Sun Protection Measures. Spending time in the sun increases your risk of skin cancer and early skin aging.

To decrease this risk, regularly use a sunscreen with a Broad Spectrum SPF value of 15 or higher and other sun protection measures including:

Limit time in the sun, especially from 10 a.m - 2 p.m.

wear long-sleeved shirts,pants,hats and sunglasses.

Storage

Other information

Protect the product in this container from excessive heat and direct sun

Avoid contact with fabrics

Inactive ingredients

Aqua(Water), Glycerin, C12-15 alkyl bezoate, Butyrospermum parkii (Shea) butter, Isostearyl isostearate, Cyclopentasiloxane, Dimethicone, Cyclohexasiloxane, Glyeryl stearate, Tribehenin, Cetearyl alcohol, PEG-100 stearate, Ammonium acryloyldimethyltaurate/VP copolymer, Silica, Phenoxyethanol, Myristyl myristate, Rosa canina fruit oil, Dimethiconol, Butylene glycol, Methylparaben, Parfum(Fragrance), Xanthan gum, Ethylparaben, Sodium lauroyl lactylate, Ascorbyl glucoside, Retinyl palmitate, Diospyros kaki calyx extract, Cholesterol, Tetrasodium EDTA, T-butyl alcohol, Lupinus albus seed extract, Propylene glycol, Carbomer, Potassium hydroxide, Ceramide 3, Ethylhexylglycerin, Polysorbate 20, Ceramide 6 ll, Phytosphingosine, Tocopherol, Triethyl citrate, Palmitoyl tripeptide-1, Palmitoyl tetrapeptide-7, Ceramide 1, CI77891(Titanium dioxide) CI 77491(Iron oxides), CI14700(Red 4)

PATIENT COUNSELING INFORMATION

Boots England NG2 3AA

Dist. in the USA by Boots Retail USA Inc.

New York NY 10005

Made in the UK

www.boots.com/no7

Description Section

No7 Lift and Luminate Triple Action Day Cream Sunscreen Broad Spectrum SPF 30 Trial Size

Discover No7's Lift and Luminate Triple Action Day Cream, supercharged with technology from our clinically proven Triple Action Serum. Targets the three key signs of ageing in older skin to reveeal younger looking skin in just 2 weeks.

Protects skin to help slow doen future signs of ageing.

Suitable for Sensitive Skin

For Best Results: Use every morning. Massage in small upward circles over your face and neck after applying your Lift and Luminate Triple Action Serum

Powered by Matrixyl 3000 Plus

Carton